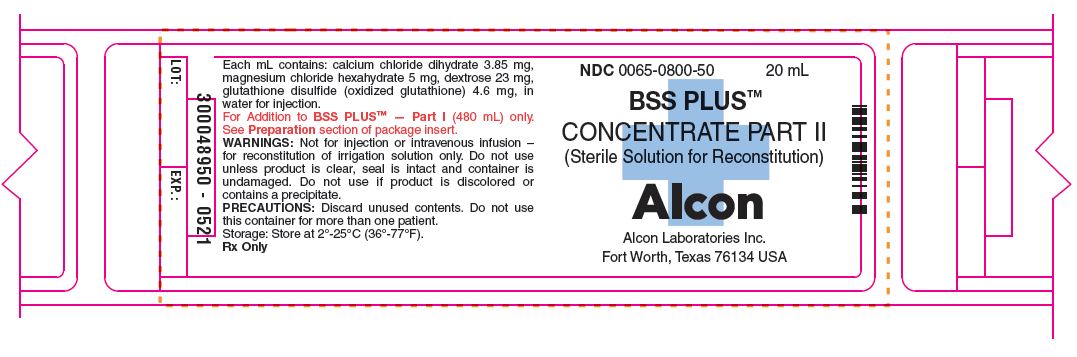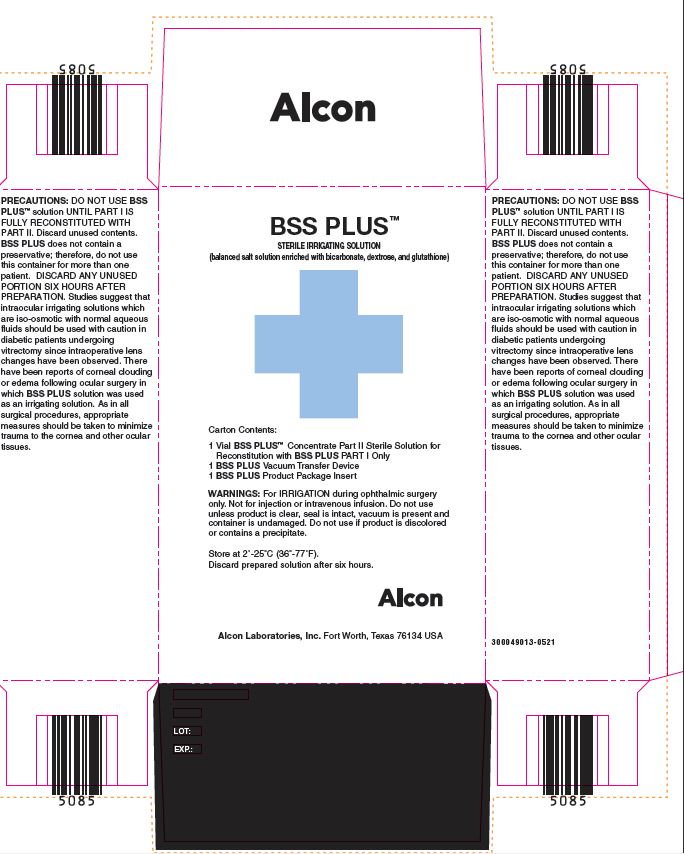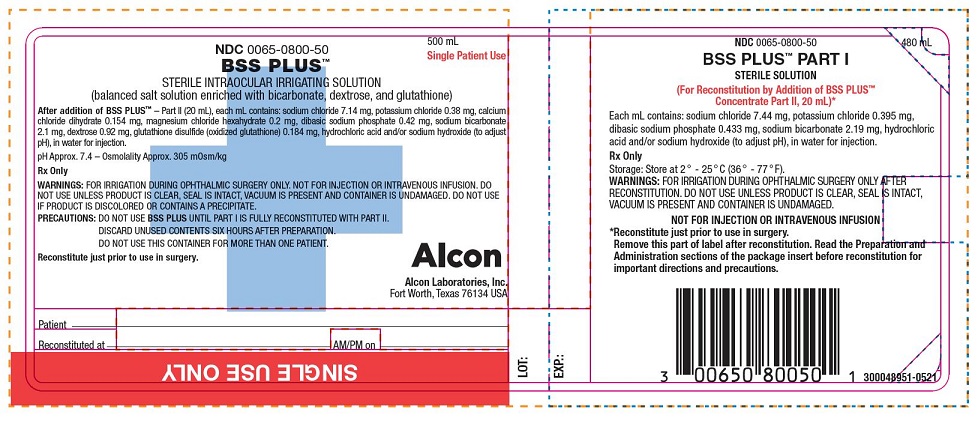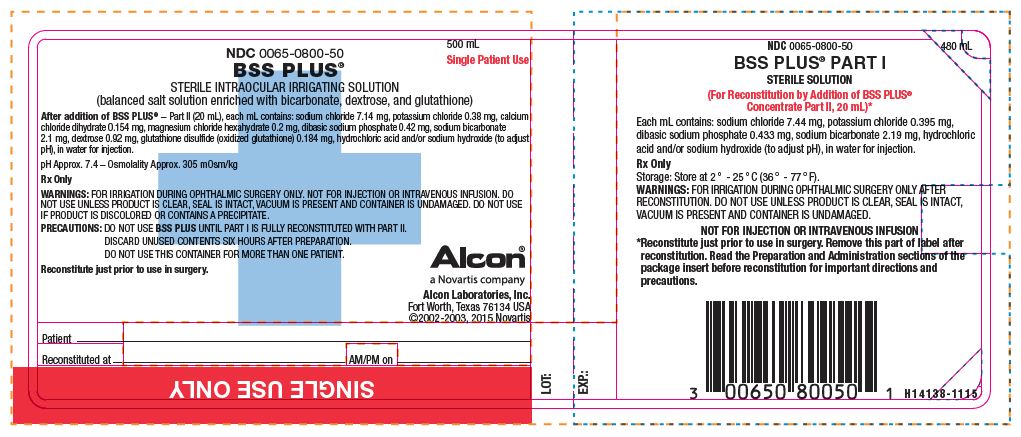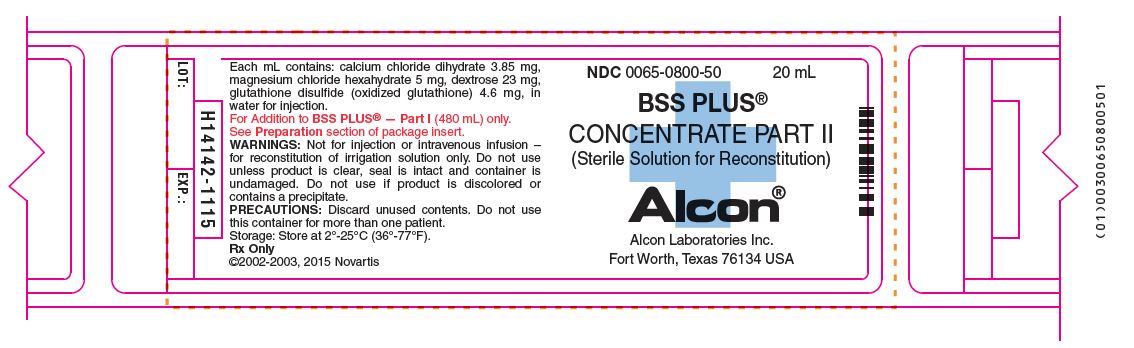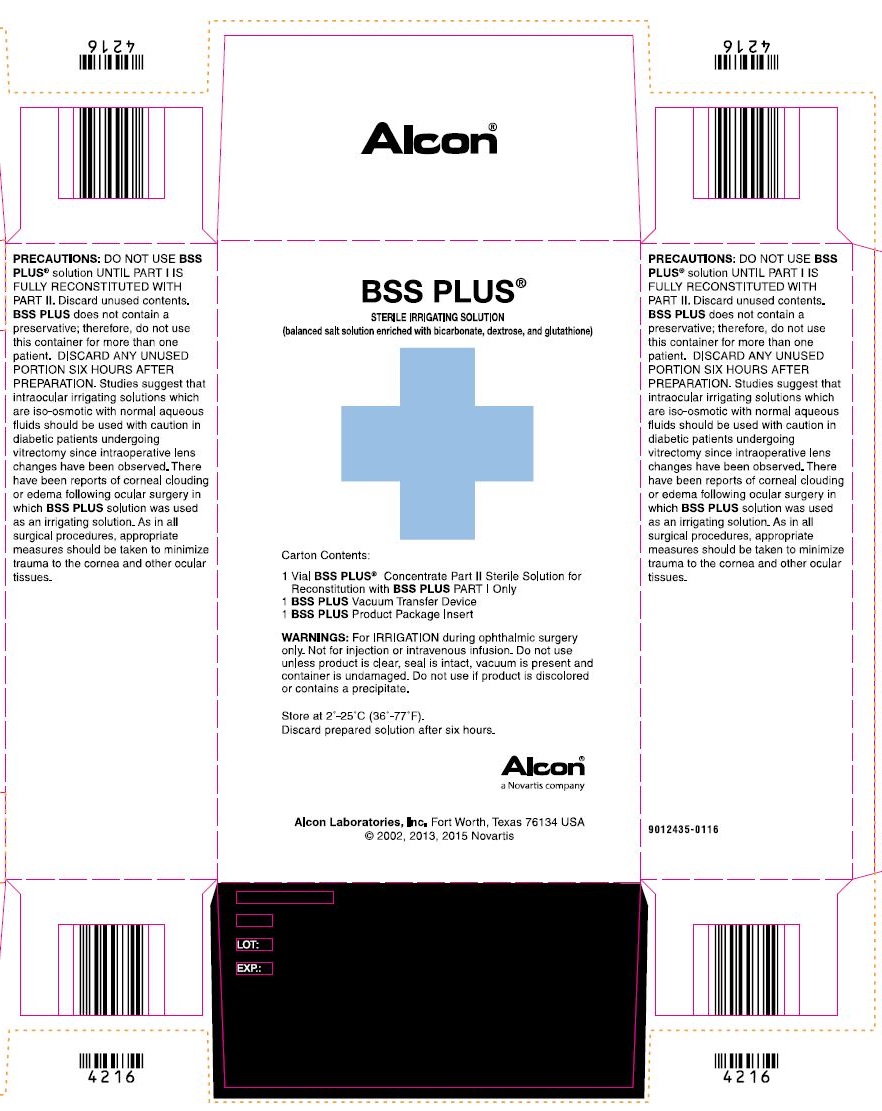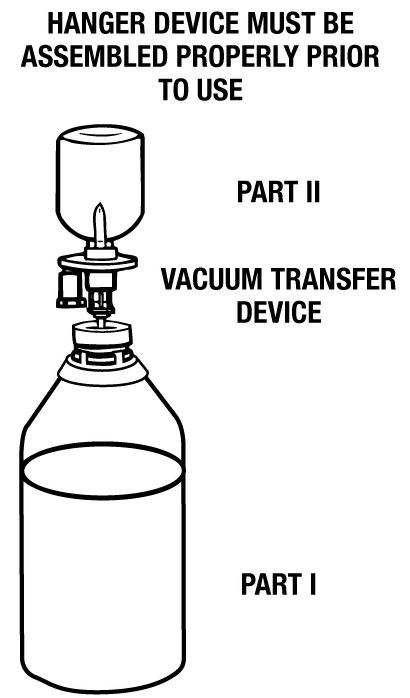 DRUG LABEL: BSS PLUS 
NDC: 0065-0800 | Form: KIT | Route: OPHTHALMIC
Manufacturer: Alcon Laboratories, Inc.
Category: prescription | Type: HUMAN PRESCRIPTION DRUG LABEL
Date: 20240125

ACTIVE INGREDIENTS: Sodium Chloride 7.44 mg/1 mL; Potassium Chloride 0.395 mg/1 mL; Sodium Phosphate, Dibasic, Unspecified Form 0.433 mg/1 mL; Sodium Bicarbonate 2.19 mg/1 mL; Calcium Chloride 3.85 mg/1 mL; Magnesium Chloride 5 mg/1 mL; Dextrose, Unspecified Form 23 mg/1 mL; Oxiglutatione 4.6 mg/1 mL
INACTIVE INGREDIENTS: Hydrochloric Acid; Sodium Hydroxide; Water; Water

BSS PLUS®
STERILE INTRAOCULAR IRRIGATING SOLUTION
(balanced salt solution enriched with bicarbonate, dextrose, and glutathione)

DESCRIPTION

DESCRIPTION: BSS PLUS® is a sterile intraocular irrigating solution for use during all intraocular surgical procedures, including those requiring a relatively long intraocular perfusion time (e.g., pars plana vitrectomy, phacoemulsification, extracapsular cataract extraction/lens aspiration, anterior segment reconstruction, etc.). The solution does not contain a preservative and should be prepared just prior to use in surgery.

Part I: Part I is a sterile 480 mL solution in a 500 mL single-dose bottle to which the Part II concentrate is added. Each mL of Part I contains: sodium chloride 7.44 mg, potassium chloride 0.395 mg, dibasic sodium phosphate 0.433 mg, sodium bicarbonate 2.19 mg, hydrochloric acid and/or sodium hydroxide (to adjust pH), in water for injection.

Part II: Part II is a sterile concentrate in a 20 mL single-dose vial for addition to Part I. Each mL of Part II contains: calcium chloride dihydrate 3.85 mg, magnesium chloride hexahydrate 5 mg, dextrose 23 mg, glutathione disulfide (oxidized glutathione) 4.6 mg, in water for injection.

After addition of BSS PLUS Part II to the Part I bottle, each mL of the reconstituted product contains: sodium chloride 7.14 mg, potassium chloride 0.38 mg, calcium chloride dihydrate 0.154 mg, magnesium chloride hexahydrate 0.2 mg, dibasic sodium phosphate 0.42 mg, sodium bicarbonate 2.1 mg, dextrose 0.92 mg, glutathione disulfide (oxidized glutathione) 0.184 mg, hydrochloric acid and/or sodium hydroxide (to adjust pH), in water for injection.

The reconstituted product has a pH of approximately 7.4. Osmolality is approximately 305 mOsm.

CLINICAL PHARMACOLOGY:

None of the components of BSS PLUS are foreign to the eye. Human perfused cornea studies have shown BSS PLUS to be an effective irrigation solution for providing corneal detumescence and maintaining corneal endothelial integrity during intraocular perfusion. An in vivo study in rabbits has shown that BSS PLUS is more suitable than normal saline or Balanced Salt Solution for intravitreal irrigation because BSS PLUS contains the appropriate bicarbonate, pH, and ionic composition necessary for the maintenance of normal retinal electrical activity. Human in vivo studies have demonstrated BSS PLUS to be safe and effective when used during surgical procedures such as pars plana vitrectomy, phacoemulsification, cataract extraction/lens aspiration, anterior segment reconstruction. No differences have been observed between adults and pediatric patients following use of this drug product.

INDICATIONS AND USAGE: BSS PLUS is indicated for use as an intraocular irrigating solution during intraocular surgical procedures involving perfusion of the eye.

CONTRAINDICATIONS

CONTRAINDICATIONS: There are no specific contraindications to the use of BSS PLUS; however, contraindications for the surgical procedure during which BSS PLUS is to be used should be strictly adhered to.

WARNINGS

WARNINGS: For IRRIGATION during ophthalmic surgery only. Not for injection or intravenous infusion. Do not use unless product is clear, seal is intact, vacuum is present and container is undamaged. Do not use if product is discolored or contains a precipitate.

PRECAUTIONS

PRECAUTIONS: DO NOT USE BSS PLUS UNTIL PART I IS FULLY RECONSTITUTED WITH PART II. Discard unused contents. BSS PLUS does not contain a preservative; therefore, do not use this container for more than one patient. DISCARD ANY UNUSED PORTION SIX HOURS AFTER PREPARATION. Studies suggest that intraocular irrigating solutions which are iso-osmotic with normal aqueous fluids should be used with caution in diabetic patients undergoing vitrectomy since intraoperative lens changes have been observed.

There have been reports of corneal clouding or edema following ocular surgery in which BSS PLUS was used as an irrigating solution. As in all surgical procedures appropriate measures should be taken to minimize trauma to the cornea and other ocular tissues.

Preparation: Reconstitute BSS PLUS® Intraocular Irrigating Solution just prior to use in surgery. Follow the same strict aseptic procedures in the reconstitution of BSS PLUS as is used for intravenous additives. Remove the blue flip-off seal from the BSS PLUS Part I (480 mL) bottle. Remove the blue flip-off seal from the BSS PLUS Part II (20 mL) vial. Clean and disinfect the rubber stoppers on both containers by using sterile alcohol wipes. Transfer the contents of the Part II vial to the Part I bottle using a BSS PLUS Vacuum Transfer Device (provided). An alternative method of solution transfer may be accomplished by using a 20 mL syringe to remove the Part II solution from the vial and transferring exactly 20 mL to the Part I container through the outer target area of the rubber stopper. An excess volume of Part II is provided in each vial. Gently agitate the contents to mix the solution. Place a sterile cap on the bottle. Remove the tear-off portion of the label. Record the time and date of reconstitution and the patient's name on the bottle label.

GERIATRIC USE

Geriatric Use: No overall differences in safety or effectiveness have been observed between elderly and younger patients.

ADVERSE REACTIONS

ADVERSE REACTIONS: Postoperative inflammatory reactions as well as incidents of corneal edema and corneal decompensation have been reported. Their relationship to the use of BSS PLUS has not been established.

DOSAGE AND ADMINISTRATION: The solution should be used according to the standard technique employed by the operating surgeon. Use an administration set with an air-inlet in the plastic spike since the bottle does not contain a separate airway tube. Follow the directions for the particular administration set to be used. Insert the spike aseptically into the bottle through the center target area of the rubber stopper. Allow the fluid to flow to remove air from the tubing before intraocular irrigation begins. If a second bottle is necessary to complete the surgical procedure, ensure that the vacuum is vented from the second bottle BEFORE attachment to the administration set.

HOW SUPPLIED

HOW SUPPLIED: BSS PLUS is supplied in two packages for reconstitution prior to use: a 500 mL glass bottle containing 480 mL (Part I) and a 20 mL glass vial (Part II); both using grey butyl stoppers and aluminum seals with polypropylene flip-off caps. See the PRECAUTIONS section regarding reconstitution of the solution.
NDC 0065-0800-50.
Storage: Store Part I and Part II at 2˚C to 25˚C (36°F to 77° F). Discard prepared solution after six hours.
Alcon
Distributed by:
Alcon Laboratories, Inc.
Fort Worth, Texas 76134 USA
©2023 Alcon, Inc.
Revised: April 2023
W300049014-0521

RECONSTITUTION INSTRUCTIONS

DIRECTIONS: Use Aseptic Technique

1. Remove the blue flip-off seal from the BSS PLUS® Part I (480 mL) bottle. Remove the blue flip-off seal from the BSS PLUS Part II (20 mL) vial. Prepare the stoppers on both parts by using sterile alcohol wipes.
2. Peel open a BSS PLUS Vacuum Transfer Device package (supplied) and remove the sterile transfer spike.
  NOTE: This device is vented permitting air to enter vial during solution transfer, thereby preventing the creation of a vacuum inside the vial. An air-inlet filter is provided to protect the system. Do not remove the air-inlet filter.
3. Remove protector from the white plastic piercing pin.
4. Firmly grasp device from behind the flange and insert the white plastic piercing pin into the upright rubber stopper of the BSS PLUS Part II (20 mL) vial.
5. Remove guard from filter needle. Firmly grasp vial in the palm of one hand and with thumb and index finger, hold plastic flange against top of vial.
6. Invert vial and immediately insert filter needle into the outer target of the rubber stopper of the BSS PLUS Part I (480 mL) bottle. (See illustration.)
7. Fluid will automatically transfer from the vial into the large vacuum bottle unless filter becomes occluded or loss of vacuum occurs. NOTE: An excess amount of BSS PLUS Part II is provided in each vial. A non-transferred solution residual of approximately 0.3 mL can be expected to remain in the vial.
8. Immediately remove needle from the BSS PLUS Part I container and discard it after solution transfer has been completed.
9. Place a sterile safety cap over the rubber stopper of Part I if the solution is not going to be used immediately. Mix the solution gently until uniform. Peel off the right-hand side of Part I bottle label (fully reconstituted BSS PLUS Solution). Record the patient’s name and the date and time of reconstitution. BSS PLUS Solution is now ready for use.

CAUTION: Reconstituted BSS PLUS Solution must be used within six hours of mixing. Discard any solution which has aged beyond that time. Never use the same bottle of BSS PLUS Solution on more than one patient.

Alternative Transfer Method
If preferred, the contents of the BSS PLUS Part II component may be aspirated with an 18-gauge cannula attached to a 20 mL syringe and then transferred into the Part I bottle.

Alcon
Distributed by:
Alcon Laboratories, Inc.
Fort Worth, Texas 76134 USA
Revised: April 2023

PRINCIPAL DISPLAY PANEL

NDC 0065-0800-50
500 mL
Single Patient Use
BSS PLUS™
STERILE INTRAOCULAR IRRIGATING SOLUTION
(balanced salt solution enriched with bicarbonate, dextrose, and glutathione)
After addition of BSS PLUS™– Part II (20 mL), each mL contains: sodium chloride 7.14 mg, potassium chloride 0.38 mg, calcium chloride dihydrate 0.154 mg, magnesium chloride hexahydrate 0.2 mg, dibasic sodium phosphate 0.42 mg, sodium bicarbonate 2.1 mg, dextrose 0.92 mg, glutathione disulfide (oxidized glutathione) 0.184 mg, hydrochloric acid and/or sodium hydroxide (to adjust pH), in water for injection.
pH Approx. 7.4 – Osmolality Approx. 305 mOsm/kg
Rx Only
WARNINGS: FOR IRRIGATION DURING OPHTHALMIC SURGERY ONLY. NOT FOR INJECTION OR INTRAVENOUS INFUSION. DO NOT USE UNLESS PRODUCT IS CLEAR, SEAL IS INTACT, VACUUM IS PRESENT AND CONTAINER IS UNDAMAGED. DO NOT USE IF PRODUCT IS DISCOLORED OR CONTAINS A PRECIPITATE.
PRECAUTIONS: DO NOT USE BSS PLUS UNTIL PART I IS FULLY RECONSTITUTED WITH PART II.
DISCARD UNUSED CONTENTS SIX HOURS AFTER PREPARATION.
DO NOT USE THIS CONTAINER FOR MORE THAN ONE PATIENT.
Reconstitute just prior to use in surgery.
Alcon
Alcon Laboratories, Inc.
Fort Worth, Texas 76134 USA
Patient_____________________
Reconstituted at _________________ AM/PM on_________________
LOT:
EXP.:
SINGLE USE ONLY
NDC 0065-0800-50
480 mL
BSS PLUS™ PART I
STERILE SOLUTION
(For Reconstitution by Addition of BSS PLUSTM Concentrate Part II, 20 mL)*
Each mL contains: sodium chloride 7.44 mg, potassium chloride 0.395 mg, dibasic sodium phosphate 0.433 mg, sodium bicarbonate 2.19 mg, hydrochloric acid and/or sodium hydroxide (to adjust pH), in water for injection.
Rx Only
Storage: Store at 2° - 25°C (36° - 77°F).
WARNINGS: FOR IRRIGATION DURING OPHTHALMIC SURGERY ONLY AFTER RECONSTITUTION. DO NOT USE UNLESS PRODUCT IS CLEAR, SEAL IS INTACT, VACUUM IS PRESENT AND CONTAINER IS UNDAMAGED.
NOT FOR INJECTION OR INTRAVENOUS INFUSION
*Reconstitute just prior to use in surgery. Remove this part of label after reconstitution. Read the Preparation and Administration sections of the package insert before reconstitution for important directions and precautions.
300048951-0521

NDC 0065-0800-50
500 mL
Single Patient Use
BSS PLUS®
STERILE INTRAOCULAR IRRIGATING SOLUTION
(balanced salt solution enriched with bicarbonate, dextrose, and glutathione)
After addition of BSS PLUS®– Part II (20 mL), each mL contains: sodium chloride 7.14 mg, potassium chloride 0.38 mg, calcium chloride dihydrate 0.154 mg, magnesium chloride hexahydrate 0.2 mg, dibasic sodium phosphate 0.42 mg, sodium bicarbonate 2.1 mg, dextrose 0.92 mg, glutathione disulfide (oxidized glutathione) 0.184 mg, hydrochloric acid and/or sodium hydroxide (to adjust pH), in water for injection.
pH Approx. 7.4 – Osmolality Approx. 305 mOsm/kg
Rx Only
WARNINGS: FOR IRRIGATION DURING OPHTHALMIC SURGERY ONLY. NOT FOR INJECTION OR INTRAVENOUS INFUSION. DO NOT USE UNLESS PRODUCT IS CLEAR, SEAL IS INTACT, VACUUM IS PRESENT AND CONTAINER IS UNDAMAGED. DO NOT USE IF PRODUCT IS DISCOLORED OR CONTAINS A PRECIPITATE.
PRECAUTIONS: DO NOT USE BSS PLUS UNTIL PART I IS FULLY RECONSTITUTED WITH PART II.
DISCARD UNUSED CONTENTS SIX HOURS AFTER PREPARATION.
DO NOT USE THIS CONTAINER FOR MORE THAN ONE PATIENT.
Reconstitute just prior to use in surgery.
Alcon®
a Novartis company
Alcon Laboratories, Inc.
Fort Worth, Texas 76134 USA
©2002-2003, 2015 Novartis
Patient_____________________
Reconstituted at _________________ AM/PM on_________________
LOT:
EXP.:
SINGLE USE ONLY

NDC 0065-0800-50
480 mL
BSS PLUS® PART I
STERILE SOLUTION
(For Reconstitution by Addition of BSS PLUS® Concentrate Part II, 20 mL)*
Each mL contains: sodium chloride 7.44 mg, potassium chloride 0.395 mg, dibasic sodium phosphate 0.433 mg, sodium bicarbonate 2.19 mg, hydrochloric acid and/or sodium hydroxide (to adjust pH), in water for injection.
Rx Only
Storage: Store at 2° - 25°C (36° - 77°F).
WARNINGS: FOR IRRIGATION DURING OPHTHALMIC SURGERY ONLY AFTER RECONSTITUTION. DO NOT USE UNLESS PRODUCT IS CLEAR, SEAL IS INTACT, VACUUM IS PRESENT AND CONTAINER IS UNDAMAGED.
NOT FOR INJECTION OR INTRAVENOUS INFUSION
*Reconstitute just prior to use in surgery. Remove this part of label after reconstitution. Read the Preparation and Administration sections of the package insert before reconstitution for important directions and precautions.
H14138-1115

NDC 0065-0800-50
20 mL
BSS PLUS®
CONCENTRATE PART II
(Sterile Solution for Reconstitution)
Alcon®
Alcon Laboratories Inc.
Fort Worth, Texas 76134 USA
Each mL contains: calcium chloride dihydrate 3.85 mg, magnesium chloride hexahydrate 5 mg, dextrose 23 mg, glutathione disulfide (oxidized glutathione) 4.6 mg, in water for injection.
For Addition to BSS PLUS® — Part I (480 mL) only.
See Preparation section of package insert.
WARNINGS: Not for injection or intravenous infusion – for reconstitution of irrigation solution only. Do not use unless product is clear, seal is intact and container is undamaged. Do not use if product is discolored or contains a precipitate.
PRECAUTIONS: Discard unused contents. Do not use this container for more than one patient.
Storage: Store at 2°-25°C (36°-77°F).
Rx Only
©2002-2003, 2015 Novartis
H14142-1115
LOT:
EXP.:

NDC 0065-0800-50
20 mL
BSS PLUS®
CONCENTRATE PART II
(Sterile Solution for Reconstitution)
Alcon®
Alcon Laboratories Inc.
Fort Worth, Texas 76134 USA
Each mL contains: calcium chloride dihydrate 3.85 mg, magnesium chloride hexahydrate 5 mg, dextrose 23 mg, glutathione disulfide (oxidized glutathione) 4.6 mg, in water for injection.
For Addition to BSS PLUS® — Part I (480 mL) only.
See Preparation section of package insert.
WARNINGS: Not for injection or intravenous infusion – for reconstitution of irrigation solution only. Do not use unless product is clear, seal is intact and container is undamaged. Do not use if product is discolored or contains a precipitate.
PRECAUTIONS: Discard unused contents. Do not use this container for more than one patient.
Storage: Store at 2°-25°C (36°-77°F).
Rx Only
©2002-2003, 2015 Novartis
H14142-1115
LOT:
EXP.:

BSS Plus™
STERILE IRRIGATING SOLUTION
(balanced salt solution enriched with bicarbonate, dextrose, and glutathione)
Carton Contents:
1 Vial BSS PLUS™ Concentrate Part II Sterile Solution for Reconstitution with BSS PLUS Part I Only
1 BSS PLUS Vacuum Transfer Device
1 BSS PLUS Product Package Insert
WARNINGS: For IRRIGATION during ophthalmic surgery only. Not for injection or intravenous infusion. Do not use unless product is clear, seal is intact, vacuum is present and container is undamaged. Do not use if product is discolored or contains a precipitate.
Store at 2°-35°C (36°-77°F).
Discard prepared solution after six hours.
Alcon
Alcon Laboratories Inc. Fort Worth, Texas 76134 USA
PRECAUTIONS: DO NOT USE BSS PLUS™ solution UNTIL PART I IS FULLY RECONSTITUTED WITH PART II. Discard unused contents. BSS PLUS does not contain a preservative; therefore, do not use this container for more than one patient. DISCARD ANY UNUSED PORTION SIX HOURS AFTER PREPARATION. Studies suggest that intraocular irrigating solutions which are iso-osmotic with normal aqueous fluids should be used with caution in diabetic patients undergoing vitrectomy since intraoperative lens changes have been observed. There have been reports of corneal clouding or edema following ocular surgery in which BSS PLUS solution was used as an irrigating solutions. As in all surgical procedures, appropriate measures should be taken to minimize trauma to the cornea and other ocular tissues.
LOT:
EXP:
300049013-0521

BSS Plus™
STERILE IRRIGATING SOLUTION
(balanced salt solution enriched with bicarbonate, dextrose, and glutathione)
Carton Contents:
1 Vial BSS PLUS® Concentrate Part II Sterile Solution for Reconstitution with BSS PLUS Part I Only
1 BSS PLUS Vacuum Transfer Device
1 BSS PLUS Product Package Insert
WARNINGS: For IRRIGATION during ophthalmic surgery only. Not for injection or intravenous infusion. Do not use unless product is clear, seal is intact, vacuum is present and container is undamaged. Do not use if product is discolored or contains a precipitate.
Stare at 2°-35°C (36°-77°F).
Discard prepared solution after six hours.
Alcon®
a Novartis company
Alcon Laboratories Inc. Fort Worth, Texas 76134 USA
© 2002, 2013, 2015 Novartis
PRECAUTIONS: DO NOT USE BSS PLUS® solution UNTIL PART I IS FULLY RECONSTITUTED WITH PART II. Discard unused contents. BSS PLUS does not contain a preservative; therefore, do not use this container for more than one patient. DISCARD ANY UNUSED PORTION SIX HOURS AFTER PREPARATION. Studies suggest that intraocular irrigating solutions which are iso-osmotic with normal aqueous fluids should be used with caution in diabetic patients undergoing vitrectomy since intraoperative lens changes have been observed. There have been reports of corneal clouding or edema following ocular surgery in which BSS PLUS solution was used as an irrigating solutions. As in all surgical procedures, appropriate measures should be taken to minimize trauma to the cornea and other ocular tissues.
LOT:
EXP:
9012435-0116